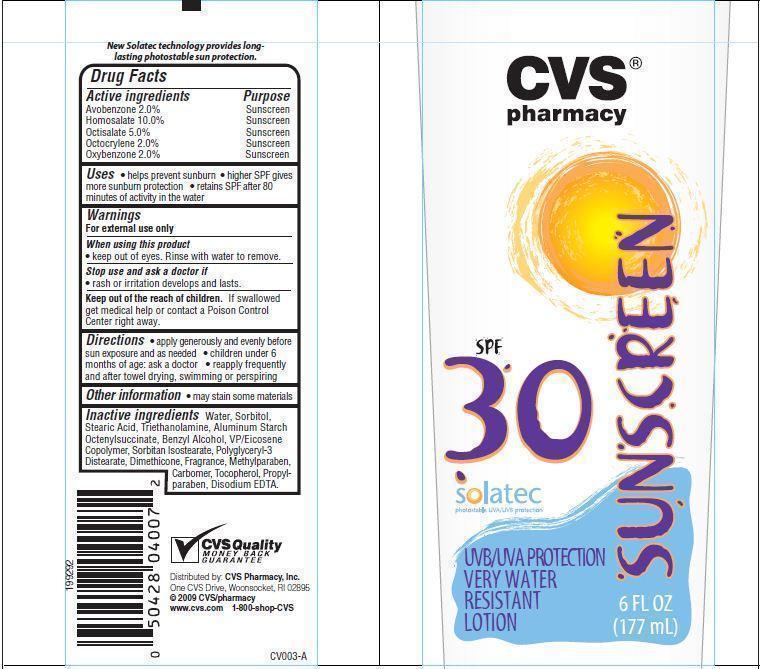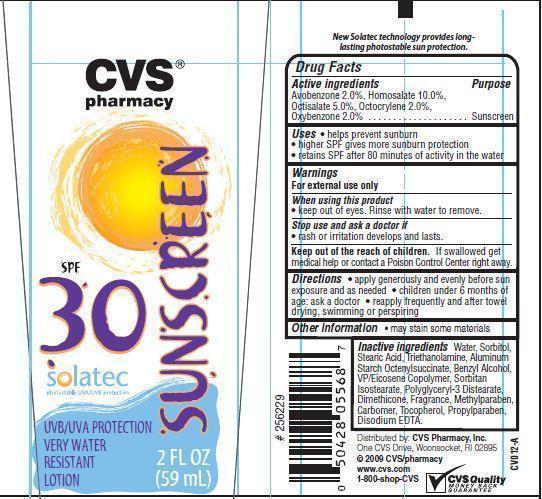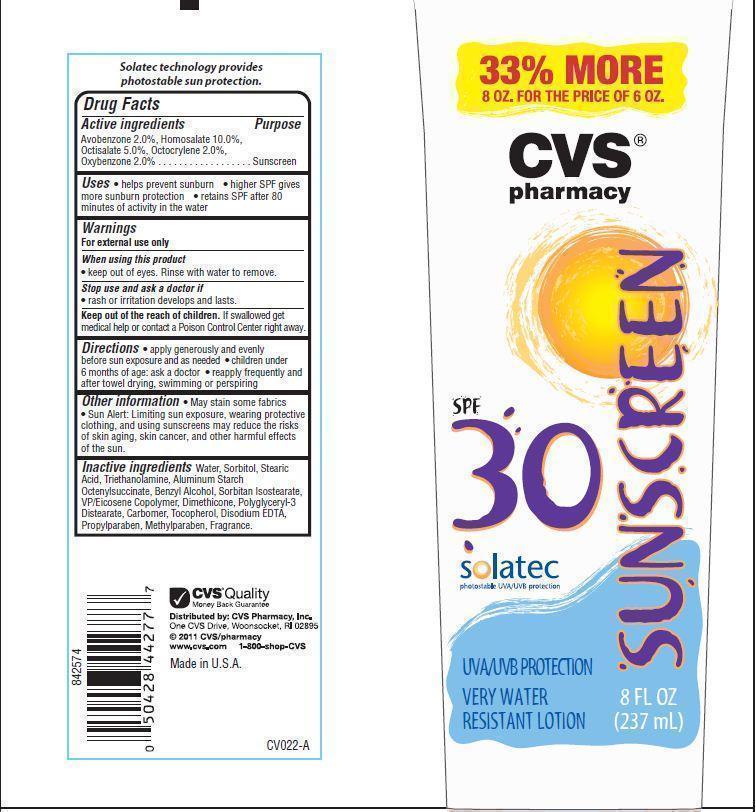 DRUG LABEL: CVS Pharmacy SPF 30
                
NDC: 59779-024 | Form: LOTION
Manufacturer: CVS Pharmacy
Category: otc | Type: HUMAN OTC DRUG LABEL
Date: 20121219

ACTIVE INGREDIENTS: AVOBENZONE 2 g/100 g; HOMOSALATE 10 g/100 g; OCTISALATE 5 g/100 g; OCTOCRYLENE 2 g/100 g; OXYBENZONE 2 g/100 g
INACTIVE INGREDIENTS: BENZYL ALCOHOL; SORBITAN ISOSTEARATE; DIMETHICONE; METHYLPARABEN; TOCOPHEROL; PROPYLPARABEN; EDETATE DISODIUM; WATER; SORBITOL; TROLAMINE; STEARIC ACID; ALUMINUM STARCH OCTENYLSUCCINATE

Drug Facts

Active ingredients

Avobenzone 2.0%
Homosalate 10.0%
Octisalate 5.0%
Octocrylene 2.0%
Oxybenzone 2.0%

Purpose

Sunscreen

Uses

- helps prevent sunburn
- higher SPF gives more sunburn protection
- retains SPF after 80 minutes of activity in water

Warnings

For external use only

When using this product

- keep out of eyes. Rinse with water to remove.

Stop use and ask a doctor if

- rash or irritation develops or lasts.

Keep out of the reach of children.
If swallowed get medical help or contact a Poison Control Center right away.

Directions

- apply generously and evenly before sun exposure and as needed
- children under 6 months of age: ask a doctor
- reapply frequently and after towel drying, swimming or perspiring

Other information

- may stain some materials

Inactive ingredients

Water, Sorbitol, Stearic Acid, Triethanolamine, Aluminum Starch Octenylsuccinate, Sorbitan Isostearate, VP/Eicosene Copolymer, Benzyl Alcohol, Dimethicone, Polyglyceryl-3 Distearate, Carbomer, Tocopherol, Disodium EDTA, Methylparaben, Propylparaben, Fragrance.

Principal Display Panel

CVS
pharmacy
SUSCREEN
SPF 30
solatec
photostable UVA/UVB protection
UVA/UVB PROTECTION
VERY WATER
RESISTANT LOTION
6 FL OZ(177 mL)
CVS
pharmacy
SUSCREEN
SPF 30
solatec
photostable UVA/UVB protection
UVA/UVB PROTECTION
VERY WATER
RESISTANT LOTION
2 FL OZ(59 mL)
33% MORE
8 OZ. FOR THE PRICE OF 6 OZ.
CVS
pharmacy
SUSCREEN
SPF 30
solatec
photostable UVA/UVB protection
UVA/UVB PROTECTION
VERY WATER
RESISTANT LOTION
8 FL OZ(237 mL)